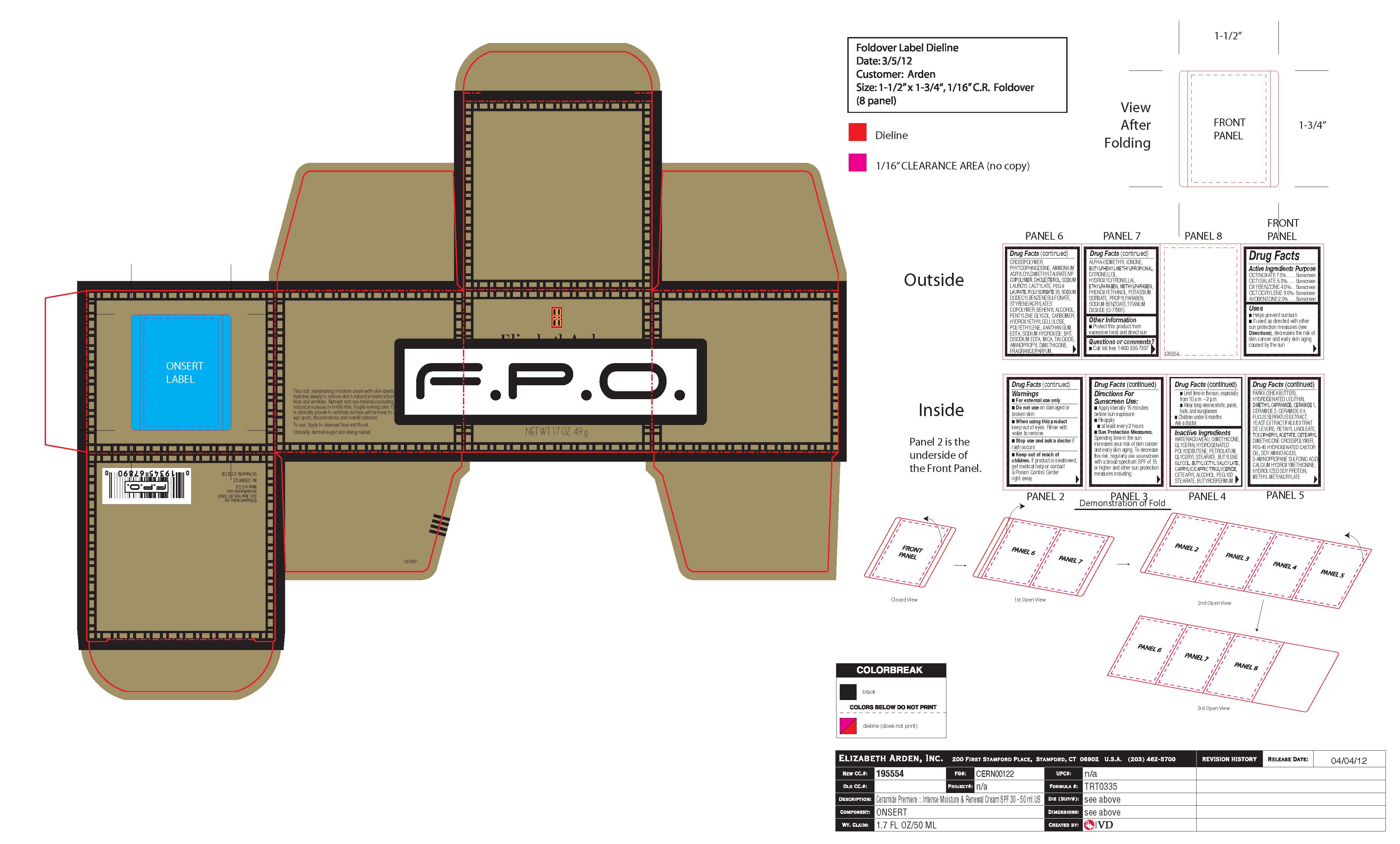 DRUG LABEL: CERAMIDE PREMIERE BROAD SPECTRUM SPF 30
NDC: 10967-669 | Form: EMULSION
Manufacturer: REVLON
Category: otc | Type: HUMAN OTC DRUG LABEL
Date: 20251229

ACTIVE INGREDIENTS: OXYBENZONE 4 mg/1 g; OCTINOXATE 7.5 mg/1 g; OCTOCRYLENE 3 mg/1 g; AVOBENZONE 2 mg/1 g; OCTISALATE 5 mg/1 g
INACTIVE INGREDIENTS: HYDROLYZED SOY PROTEIN (ENZYMATIC; 2000 MW); CHOLESTEROL; GLYCERIN; PHYTOSPHINGOSINE; ETHYLPARABEN; POTASSIUM SORBATE; POLYSORBATE 20; STANNIC OXIDE; BUTYLOCTYL SALICYLATE; XANTHAN GUM; CERAMIDE 1; FUCUS SERRATUS; EDETATE DISODIUM; AMINO ACIDS, SOY; BUTYLPHENYL METHYLPROPIONAL; DIMETHICONE; EDETIC ACID; MICA; WATER; BUTYLENE GLYCOL; MEDIUM-CHAIN TRIGLYCERIDES; DIMETHYL CAPRAMIDE; CERAMIDE 6 II; PEG-100 STEARATE; SODIUM DODECYLBENZENESULFONATE; SODIUM HYDROXIDE; PEG-8 LAURATE; TRAMIPROSATE; METHYL METHACRYLATE/GLYCOL DIMETHACRYLATE CROSSPOLYMER; AMINOPROPYL DIMETHICONE (1000 MPA.S); ISOMETHYL-.ALPHA.-IONONE; HYDROXYCITRONELLAL; CARBOMER HOMOPOLYMER, UNSPECIFIED TYPE; PROPYLPARABEN; METHYLPARABEN; DOCOSANOL; PHENOXYETHANOL; DESMENINOL CALCIUM; SODIUM BENZOATE; TITANIUM DIOXIDE; HYDROGENATED POLYBUTENE (1300 MW); PETROLATUM; GLYCERYL MONOSTEARATE; HYDROGENATED SOYBEAN LECITHIN; CERAMIDE 3; YEAST

CERAMIDE PREMIERE INTENSE MOISTURE AND RENEWAL ACTIVATION CREAM BROAD SPECTRUM SUNSCREEN SPF 30

Active Ingredients Purpose

OCTINOXATE 7.5% ....... Sunscreen
OCTISALATE 5.0%........ Sunscreen
OXYBENZONE 4.0%........ Sunscreen
OCTOCRYLENE 3.0%. ...... Sunscreen
AVOBENZONE 2.0%....... Sunscreen

Inactive Ingredients

WATER/AQUA/EAU, DIMETHICONE, GLYCERIN, HYDROGENATED POLYISOBUTENE, PETROLATUM, GLYCERYL STEARATE, BUTYLENE GLYCOL, BUTYLOCTYL SALICYLATE, CAPRYLIC/CAPRIC TRIGLYCERIDE, CETEARYL ALCOHOL, PEG-100 STEARATE, BUTYROSPERMUM PARKII (SHEA BUTTER), HYDROGENATED LECITHIN, DIMETHYL CAPRAMIDE, CERAMIDE 1, CERAMIDE 3, CERAMIDE 6 II, FUCUS SERRATUS EXTRACT, YEAST EXTRACT/FAEX/EXTRAIT DE LEVURE, RETINYL LINOLEATE, TOCOPHERYL ACETATE, CETEARYL DIMETHICONE CROSSPOLYMER, PEG-40 HYDROGENATED CASTOR OIL, SOY AMINO ACIDS, 3-AMINOPROPANE SULFONIC ACID, CALCIUM HYDROXYMETHIONINE, HYDROLYZED SOY PROTEIN, METHYL METHACRYLATE CROSSPOLYMER, PHYTOSPHINGOSINE, AMMONIUM ACRYLOYLDIMETHYLTAURATE/VP COPOLYMER, CHOLESTEROL, SODIUM LAUROYL LACTYLATE, PEG-8 LAURATE, POLYSORBATE 20, SODIUM DODECYLBENZENESULFONATE, STYRENE/ACRYLATES COPOLYMER, BEHENYL ALCOHOL, PENTYLENE GLYCOL, CARBOMER, HYDROXYETHYLCELLULOSE, POLYETHYLENE, XANTHAN GUM, EDTA, SODIUM HYDROXIDE, BHT, DISODIUM EDTA, MICA, TIN OXIDE, AMINOPROPYL DIMETHICONE, FRAGRANCE/PARFUM, ALPHA-ISOMETHYL IONONE, BUTYLPHENYL METHYLPROPIONAL, CITRONELLOL, HYDROXYCITRONELLAL, ETHYLPARABEN, METHYLPARABEN, PHENOXYETHANOL, POTASSIUM SORBATE, PROPYLPARABEN, SODIUM BENZOATE, TITANIUM DIOXIDE (CI 77891).

Uses

- Helps prevent sunburn
- If used as directed with other sun protection measures (see Directions), decreases the risk of skin cancer and early skin aging caused by the sun

Warnings

- For external use only

- Do not use on damaged or broken skin
- When using this product keep out of eyes. Rinse with water to remove.
- Stop use and ask a doctor if rash occurs
- Keep out of reach of children. If product is swallowed, get medical help or contact a Poison Control Center right away.

Directions For Sunscreen Use

- Apply liberally 15 minutes before sun exposure
- Reapply:
- at least every 2 hours

- Sun Protection Measures. Spending time in the sun increases your risk of skin cancer and early skin aging. To decrease this risk, regularly use a sunscreen with a broad spectrum SPF of 15 or higher and other sun protection measures including:

- Limit time in the sun, especially from 10 a.m. – 2 p.m.
- Wear long-sleeve shirts, pants, hats, and sunglasses

- Children under 6 months: Ask a doctor.

DOSAGE AND ADMINISTRATION

- Apply liberally 15 minutes before sun exposure
- Reapply at least every 2 hours

INDICATIONS AND USAGE

- Helps prevent sunburn
- If used as directed with other sun protection measures (see Directions), decreases the risk of skin cancer and early skin againg caused by the sun

Keep Out of Reach of Children. If product is swallowed, get medical help or contact a poison control center right away.

PURPOSE

Sunscreen